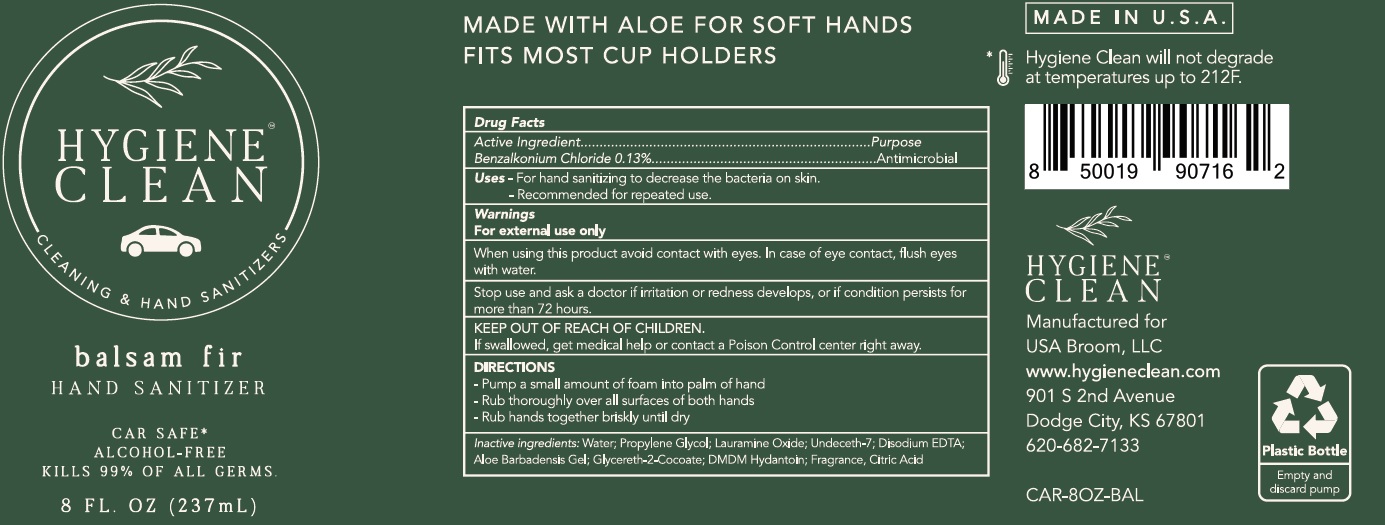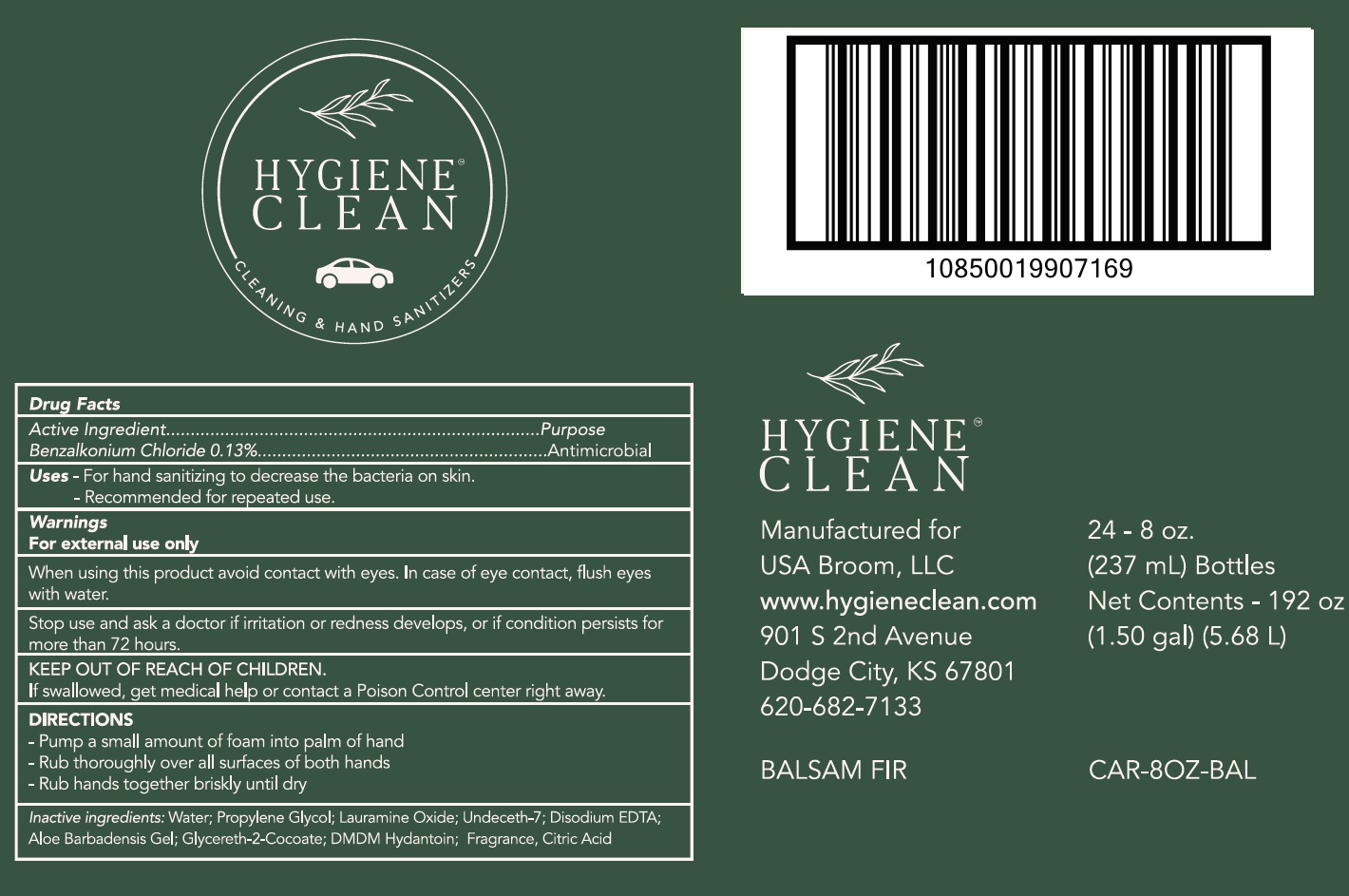 DRUG LABEL: Hygiene Clean Balsam Fir Hand Sanitizer Alcohol Free
NDC: 80499-004 | Form: LIQUID
Manufacturer: USA Broom LLC
Category: otc | Type: HUMAN OTC DRUG LABEL
Date: 20231028

ACTIVE INGREDIENTS: BENZALKONIUM CHLORIDE 1.3 mg/1 mL
INACTIVE INGREDIENTS: ALOE VERA LEAF; WATER; PROPYLENE GLYCOL; LAURAMINE OXIDE; UNDECETH-7; EDETATE DISODIUM ANHYDROUS; GLYCERETH-2 COCOATE; DMDM HYDANTOIN; CITRIC ACID MONOHYDRATE

Hygiene Clean Balsam Fir Hand Sanitizer Alcohol Free

Active Ingredient

Benzalkonium Chloride 0.13%

Purpose

Antimicrobial

Uses

- For hand sanitizing to decrease the bacteria on skin.

- Recommended for repeated use.

Warnings

For external use only

When using this product

avoid contact with eyes. In case of eye contact, flush eyes with water.

Stop use and ask a doctor

if irritation or redness develops, or if condition persists for more than 72 hours.

KEEP OUT OF REACH OF CHILDREN.

If swallowed, get medical help or contact a Poison Control center right away.

DIRECTIONS

- Pump a small amount of foam into palm of hand

- Rub thoroughly over all surfaces of both hands

- Rub hands together briskly until dry

Inactive ingredients:

Water; Propylene Glycol; Lauramine Oxide, Undeceth-7; Disodium EDTA; Aloe Barbadensis Gel; Glycereth-2-Cocoate; DMDM Hydantoin; Fragrance, Citric Acid